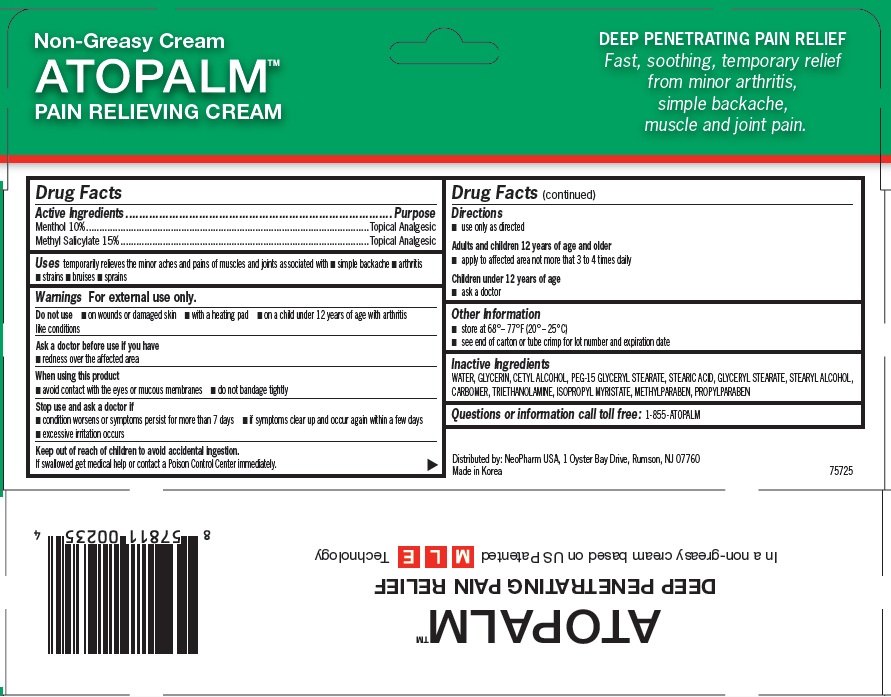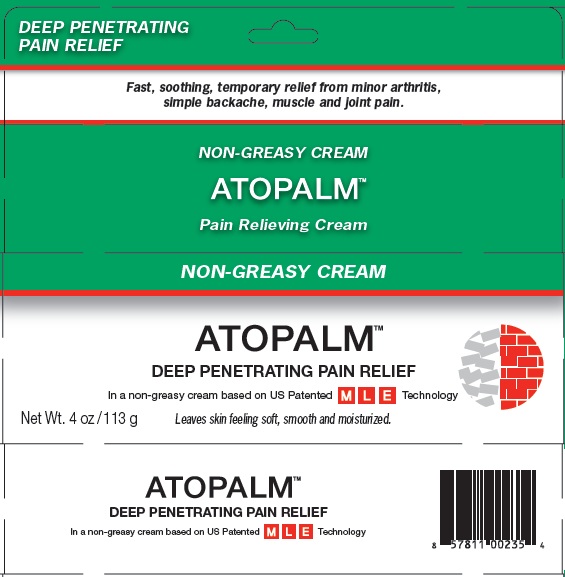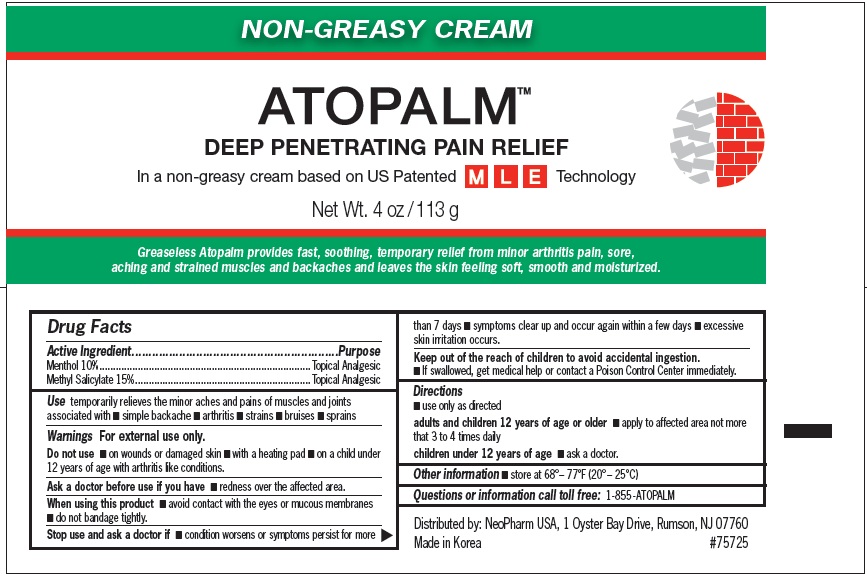 DRUG LABEL: ATOPALM Deep Penetrating Pain Relieving
NDC: 51141-0235 | Form: CREAM
Manufacturer: NeoPharm Co., Ltd.
Category: otc | Type: HUMAN OTC DRUG LABEL
Date: 20120119

ACTIVE INGREDIENTS: MENTHOL 10 g/100 g; METHYL SALICYLATE 15 g/100 g
INACTIVE INGREDIENTS: WATER; GLYCERIN; CETYL ALCOHOL; PEG-15 GLYCERYL STEARATE; STEARIC ACID; GLYCERYL MONOSTEARATE; STEARYL ALCOHOL; TROLAMINE; ISOPROPYL MYRISTATE; METHYLPARABEN; PROPYLPARABEN

ATOPALM Pain Relieving Cream

Active Ingredients

Menthol 10%
Methyl Salicylate 15%

Purpose

Topical Analgesic

Uses

temporarily relieves the minor aches and pains of muscles and joints associated with

- simple backache
- arthritis
- strains
- bruises
- sprains

Warnings

For external use only.

Do not use

- on wounds or damaged skin
- with a heating pad
- on a child under 12 years of age wih arthritis like conditions

Ask a doctor before use if you have

redness over the affected area

When using this product

- avoid contact with the eyes or mucous membranes
- do not bandage tightly

Stop use and ask a doctor if

- condition worsens or symptoms persist for more than 7 days
- if symptoms clear up and occur again within a few days
- excessive irritation occurs

Keep out of reach of children to avoid accidental ingestion.

If swallowed get medical help or contact a Poison Control Center immediately.

Directions

- use only as directed

Adults and children 12 years of age and older

- apply to affected area not more than 3 to 4 times daily

Children under 12 years of age

- ask a doctor

Other Information

- store at 68° – 77°F (20° – 25°C)
- see end of carton or tube crimp for lot number and expiration date

Inactive Ingredients

WATER, GLYCERIN, CETYL ALCOHOL, PEG-15 GLYCERYL STEARATE, STEARIC ACID, GLYCERYL STEARATE, STEARYL ALCOHOL, CARBOMER, TRIETHANOLAMINE, ISOPROPYL MYRISTATE, METHYLPARABEN, PROPYLPARABEN

Questions or information call toll free:

1-855- ATOPALM

Product Labeling

DEEP PENETRATING PAIN RELIEF

Fast, soothing, temporary relief from minor arthritis, simple backache, muscle and joint pain.

NON-GREASY CREAM
ATOPALM
Pain Relieving Cream

DEEP PENETRATING PAIN RELIEF

In a non-greasy cream based on US Patented MLE Technology
Leaves skin feeling soft, smooth and moisturized.

4 oz /113 g

Distributed by: NeoPharm USA, 1 Oyster Bay Drive, Rumson, NJ 07760
Made in Korea